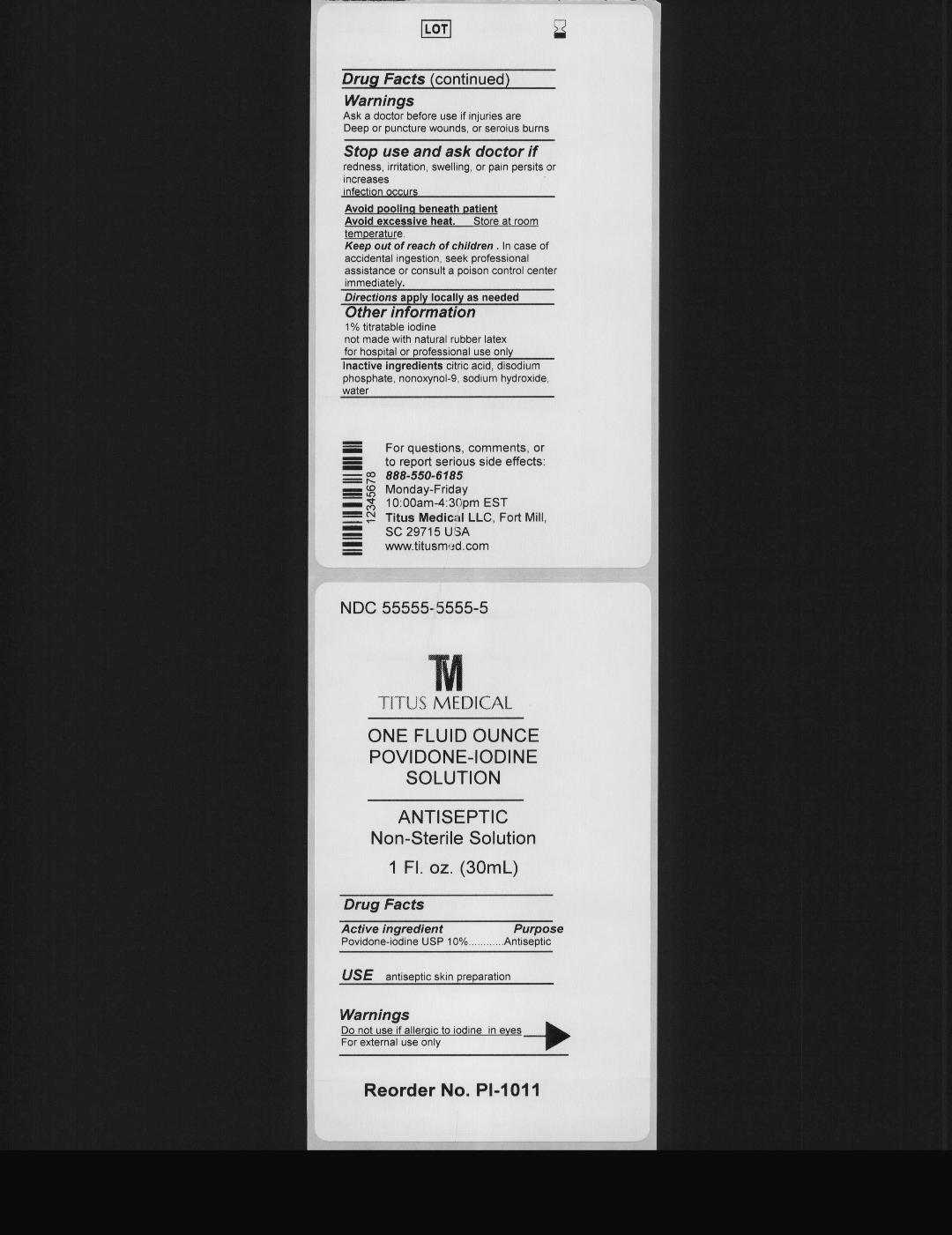 DRUG LABEL: TM TITUS MEDICAL ANTISEPTIC Non Sterile
NDC: 81526-001 | Form: SOLUTION
Manufacturer: Titus Medical LLC
Category: otc | Type: HUMAN OTC DRUG LABEL
Date: 20250117

ACTIVE INGREDIENTS: POVIDONE-IODINE 1 g/100 mL
INACTIVE INGREDIENTS: WATER; CITRIC ACID MONOHYDRATE; SODIUM PHOSPHATE, DIBASIC; NONOXYNOL-9; SODIUM HYDROXIDE

81526-001

Active Ingredient:

Povidone-Iodine USP (10%)

Purpose

Antiseptic

Use:

Antiseptic skin preparation

Warnings:

Do not use if allergic to iodine in eyes

For external use only

Avoid "pooling" beneath patients.

Avoid excessive heat. Store at room temperature.

Ask a doctor before use if injuries are deep or puncture wounds, or serious burns

Stop use and ask a doctor if

- redness, irritation, swelling, or pain persists or increases
- infection occurs

Keep out of reach of children. In case of accidental ingestion, seek professional assistance or consult a poison control center immediately

DOSAGE AND ADMINISTRATION

Apply locally as need

Other information

- 1% titratable iodine
- not made with natural rubber latex
- for hospital or professional use only

Inactive Ingredient

Citric acid, Disodium phosphate, Nonoxynol-9, Sodium hydroxide, Water